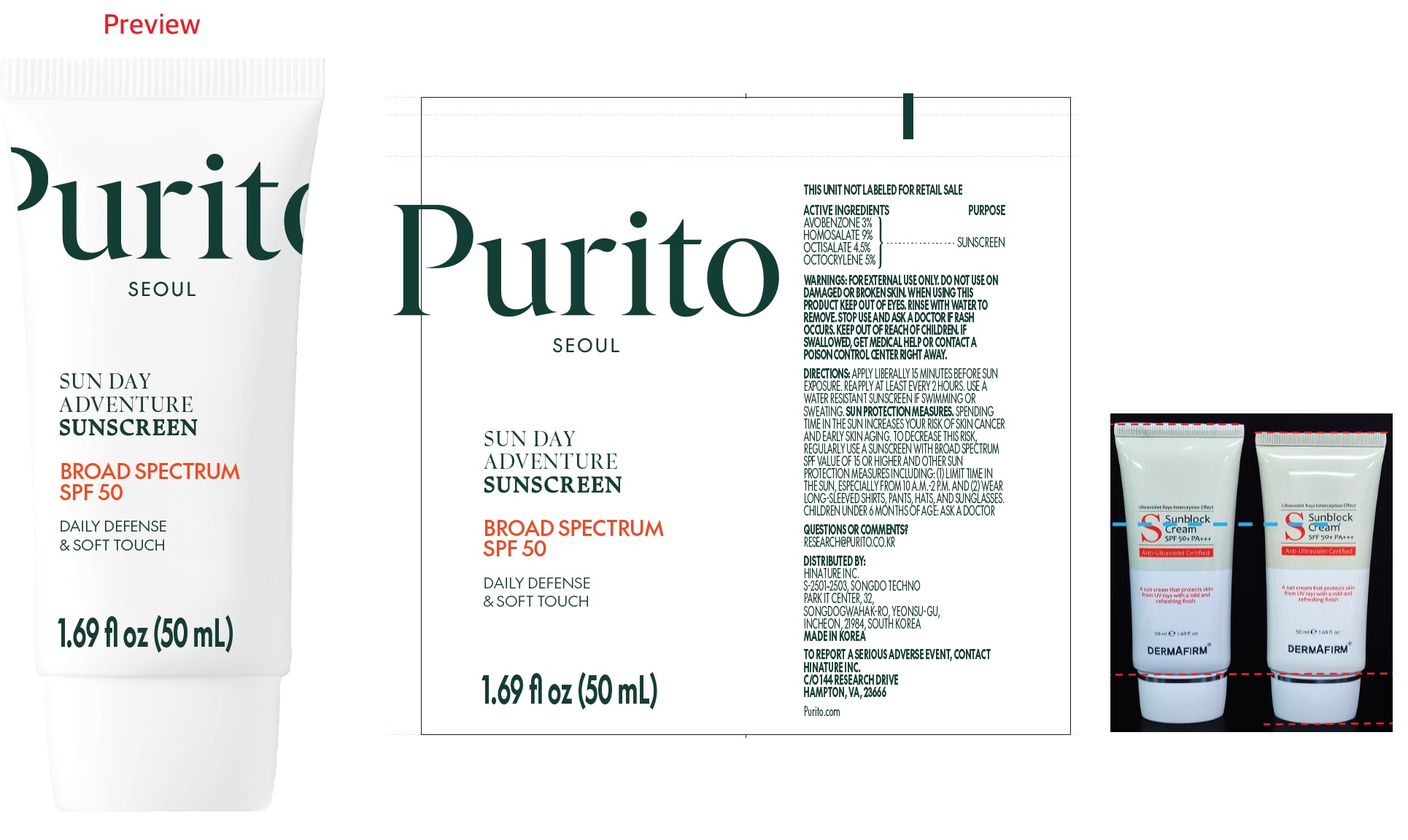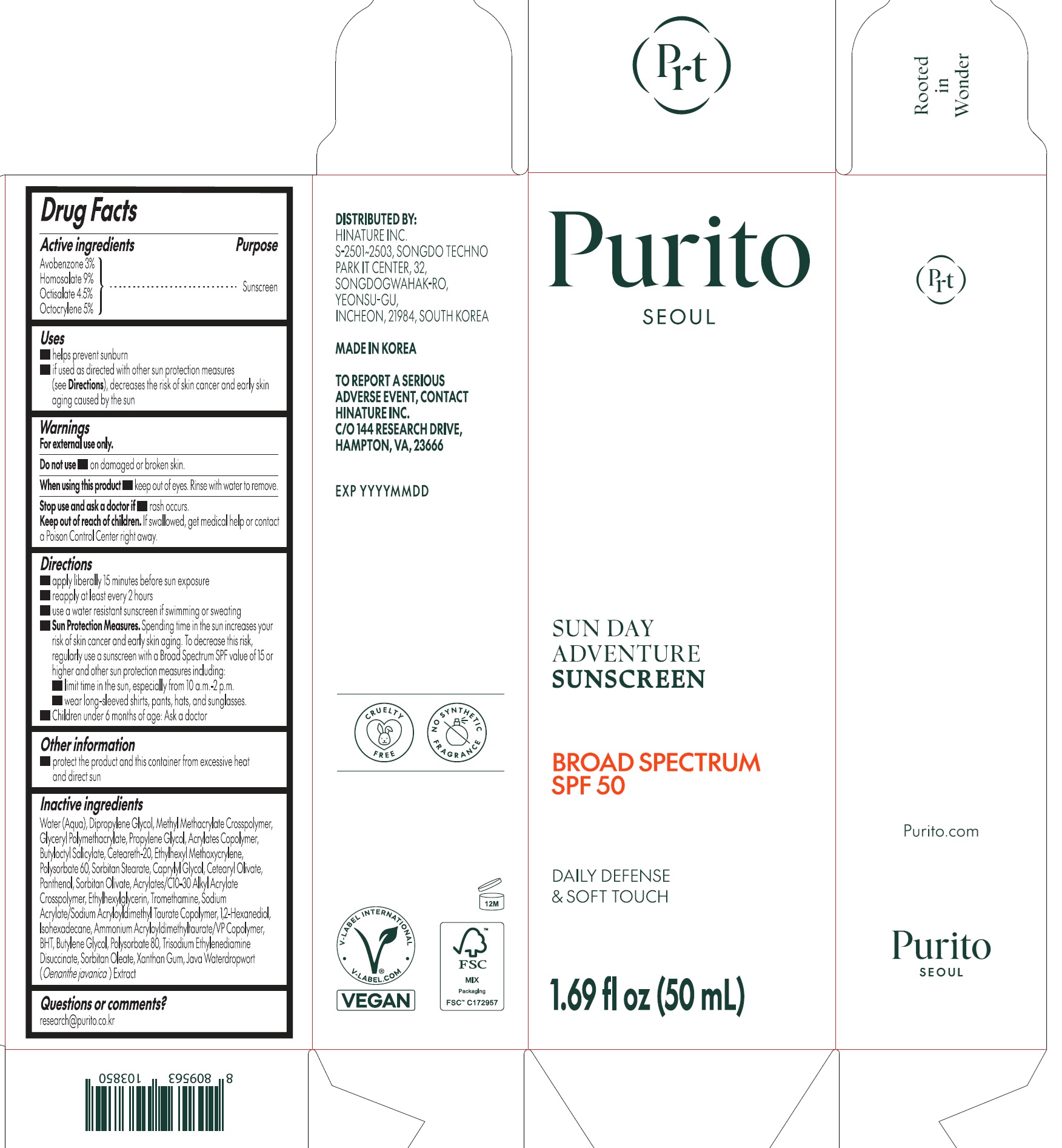 DRUG LABEL: Purito Sunday Adventure Sunscreen SPF 50, 50 mL
NDC: 73251-010 | Form: CREAM
Manufacturer: Hinature
Category: otc | Type: HUMAN OTC DRUG LABEL
Date: 20250212

ACTIVE INGREDIENTS: AVOBENZONE 30 mg/1 mL; HOMOSALATE 90 mg/1 mL; OCTISALATE 45 mg/1 mL; OCTOCRYLENE 50 mg/1 mL
INACTIVE INGREDIENTS: AMMONIUM ACRYLOYLDIMETHYLTAURATE/VP COPOLYMER; BUTYLATED HYDROXYTOLUENE; BUTYLENE GLYCOL; POLYSORBATE 80; TRISODIUM ETHYLENEDIAMINE DISUCCINATE; SORBITAN OLEATE; XANTHAN GUM; DIPROPYLENE GLYCOL; WATER; PROPYLENE GLYCOL; BUTYLOCTYL SALICYLATE; CETEARETH-20; ETHYLHEXYL METHOXYCRYLENE; POLYSORBATE 60; SORBITAN MONOSTEARATE; CAPRYLYL GLYCOL; CETEARYL OLIVATE; PANTHENOL; SORBITAN OLIVATE; ETHYLHEXYLGLYCERIN; TROMETHAMINE; 1,2-HEXANEDIOL; ISOHEXADECANE

Purito Sun Day Adventure Sunscreen SPF 50

Active ingredients

Avobenzone 3%
Homosalate 9%
Octisalate 4.5%
Octocrylene 5%

Purpose

Sunscreen

Uses

- helps prevent sunburn
- if used as directed with other sun protection measures (see Directions), decreases the risk of skin cancer and early skin aging caused by the sun

Warnings

For external use only.

Do not use

- on damaged or broken skin.

When using this product

- keep out of eyes. Rinse with water to remove.

Stop use and ask a doctor if

- rash occurs.

Keep out of reach of children.

If swallowed, get medical help or contact a Poison Control Center right away.

Directions

- apply liberally 15 minutes before sun exposure
- reapply at least every 2 hours
- use a water resistant sunscreen if swimming or sweating
- Sun Protection Measures.Spending time in the sun increases your risk of skin cancer and early skin aging. To decrease this risk, regularly use a sunscreen with a Broad Spectrum SPF value of 15 or higher and other sun protection measures including:
- limit time in the sun, especially from 10 a.m.-2 p.m.
- wear long-sleeved shirts, pants, hats, and sunglasses.
- Children under 6 months of age: Ask a doctor

Other information

- protect the product and this container from excessive heat and direct sun

Inactive ingredients

Water (Aqua), Dipropylene Glycol, Methyl Methacrylate Crosspolymer, Glyceryl Polymethacrylate, Propylene Glycol, Acrylates Copolymer, Butyloctyl Salicylate, Ceteareth-20, Ethylhexyl Methoxycrylene, Polysorbate 60, Sorbitan Stearate, Caprylyl Glycol, Cetearyl Olivate, Panthenol, Sorbitan Olivate, Acrylates/C10-30 Alkyl Acrylate Crosspolymer, Ethylhexylglycerin, Tromethamine, Sodium Acrylate/Sodium Acryloyldimethyl Taurate Copolymer, 1,2-Hexanediol, Isohexadecane, Ammonium Acryloyldimethyltaurate/VP Copolymer, BHT, Butylene Glycol, Polysorbate 80, Trisodium Ethylenediamine Disuccinate, Sorbitan Oleate, Xanthan Gum, Java Waterdropwort (Oenanthe javanica) Extract

Questions or Comments?

research@purito.co.kr